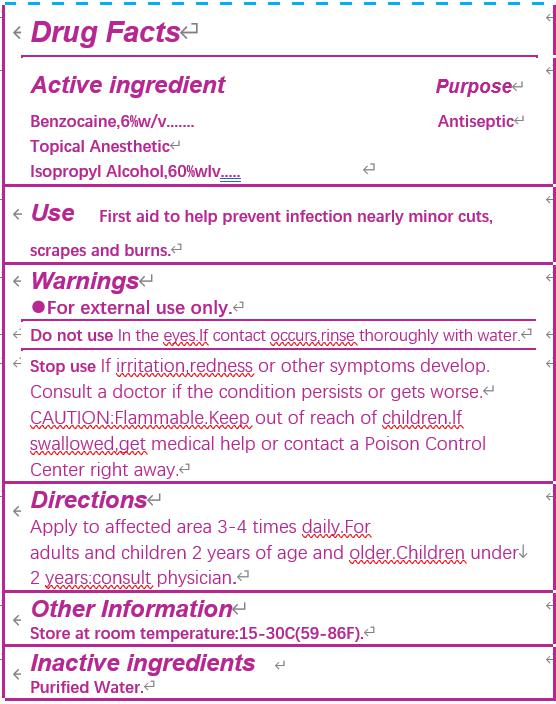 DRUG LABEL: sting relief medicated pad
NDC: 80514-005 | Form: SWAB
Manufacturer: JIANGSU HAIDA INTERNATIONAL TRADING CO., LTD.
Category: otc | Type: HUMAN OTC DRUG LABEL
Date: 20231226

ACTIVE INGREDIENTS: BENZOCAINE 6 g/100 g; ISOPROPYL ALCOHOL 60 g/100 g
INACTIVE INGREDIENTS: WATER

Active ingredient

Benzocaine 6% w/v

Isopropyl alcohol 60% w/v

Purpose

Antiseptic

Uses

First aid to help prevent infection nearly minor cuts,scrapes and burns.

Warnings

For external use only.

Do not use in the eyses.If contact occurs, rinse thoroughly with water.

Stop use if irritation,redness or other symptoms develop.

Consult a doctor if the condition persists or get worse.

CAUTION:Flammable.

Keep out of reach of children.

If swallowed, get medical help or contact a Poison Control Center right away.

Directions

Apply to affected area 3-4 times daily for adults and children 2 years of age and older.

Children under 2 years:consult physician.

Inactive ingredients

Purified water.